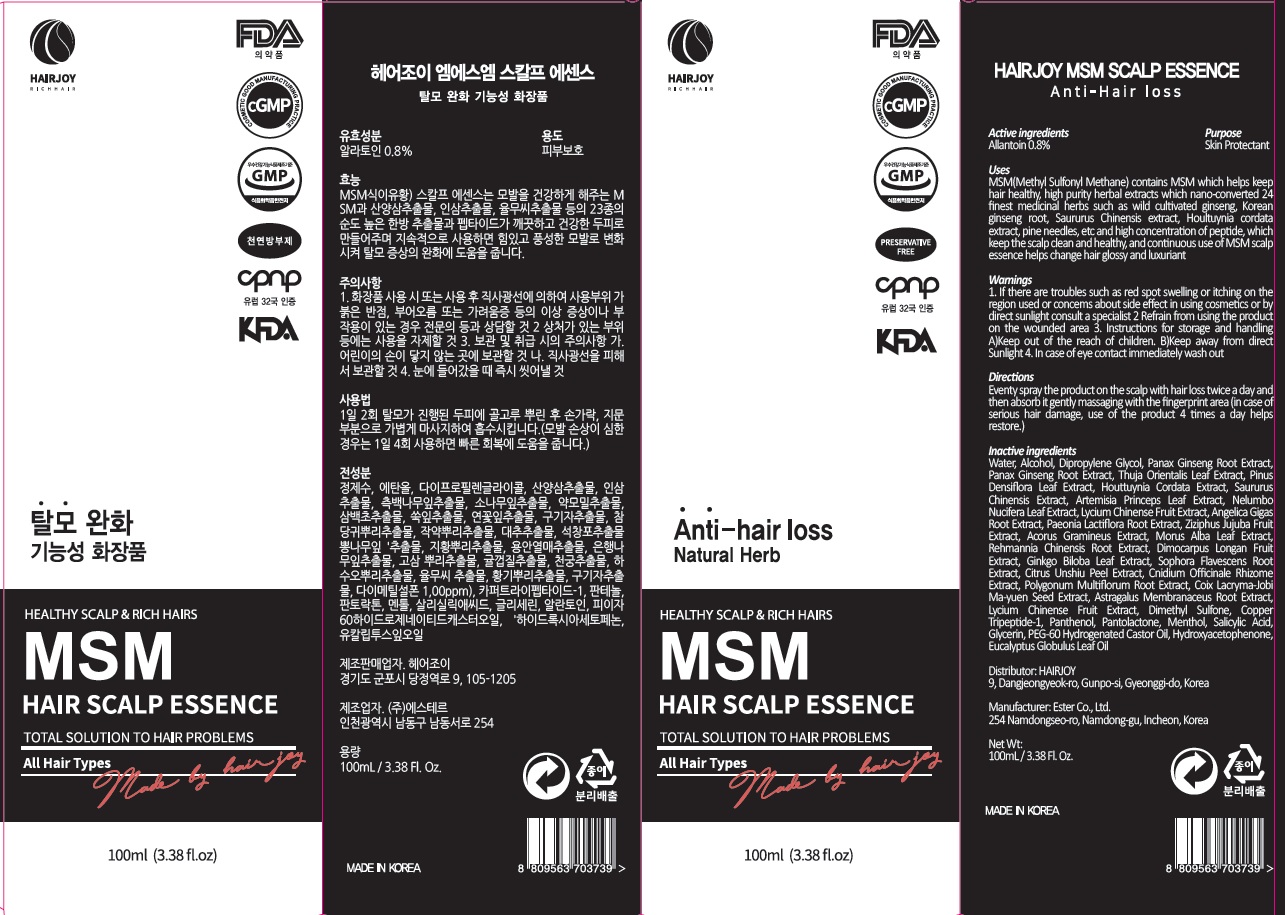 DRUG LABEL: HAIRJOY MSM SCALP ESSENCE
NDC: 69384-050 | Form: SPRAY
Manufacturer: HAIRJOY
Category: otc | Type: HUMAN OTC DRUG LABEL
Date: 20191205

ACTIVE INGREDIENTS: Allantoin 0.8 g/100 mL
INACTIVE INGREDIENTS: Water; Alcohol

ACTIVE INGREDIENT

Active ingredient: Allantoin 0.8%

INACTIVE INGREDIENT

Inactive ingredients:

Water, Alcohol, Dipropylene Glycol, Panax Ginseng Root Extract, Panax Ginseng Root Extract, Thuja Orientalis Leaf Extract, Pinus Densiflora Leaf Extract, Houttuynia Cordata Extract, Saururus Chinensis Extract, Artemisia Princeps Leaf Extract, Nelumbo Nucifera Leaf Extract, Lycium Chinense Fruit Extract, Angelica Gigas Root Extract, Paeonia Lactiflora Root Extract, Ziziphus Jujuba Fruit Extract, Acorus Gramineus Extract, Morus Alba Leaf Extract, Rehmannia Chinensis Root Extract, Dimocarpus Longan Fruit Extract, Ginkgo Biloba Leaf Extract, Sophora Flavescens Root Extract, Citrus Unshiu Peel Extract, Cnidium Officinale Rhizome Extract, Polygonum Multiflorum Root Extract, Coix Lacryma-Jobi Ma-yuen Seed Extract, Astragalus Membranaceus Root Extract, Lycium Chinense Fruit Extract, Dimethyl Sulfone, Copper Tripeptide-1, Panthenol, Pantolactone, Menthol, Salicylic Acid, Glycerin, PEG-60 Hydrogenated Castor Oil, Hydroxyacetophenone, Eucalyptus Globulus Leaf Oil

PURPOSE

Purpose: Skin Protectant

WARNINGS

1. If there are troubles such as red spot swelling or itching on the region used or concems about side effect in using cosmetics or by direct sunlight consult a specialist 2 Refrain from using the product on the wounded area 3. Instructions for storage and handling A)Keep out of the reach of children. B)Keep away from direct Sunlight 4. In case of eye contact immediately wash out

KEEP OUT OF REACH OF CHILDREN

Keep out of the reach of infants and children.

Uses

MSM(Methyl Sulfonyl Methane) contains MSM which helps keep hair healthy, high purity herbal extracts which nano-converted 24 finest medicinal herbs such as wild cultivated ginseng, Korean ginseng root, Saururus Chinensis extract, Houltuynia cordata extract, pine needles, etc and high concentration of peptide, which keep the scalp clean and healthy, and continuous use of MSM scalp essence helps change hair glossy and luxuriant

Directions

Evenly spray the product on the scalp with hair loss twice a day and then absorb it gently massaging with the fingerprint area (in case of serious hair damage, use of the product 4 times a day helps restore.)